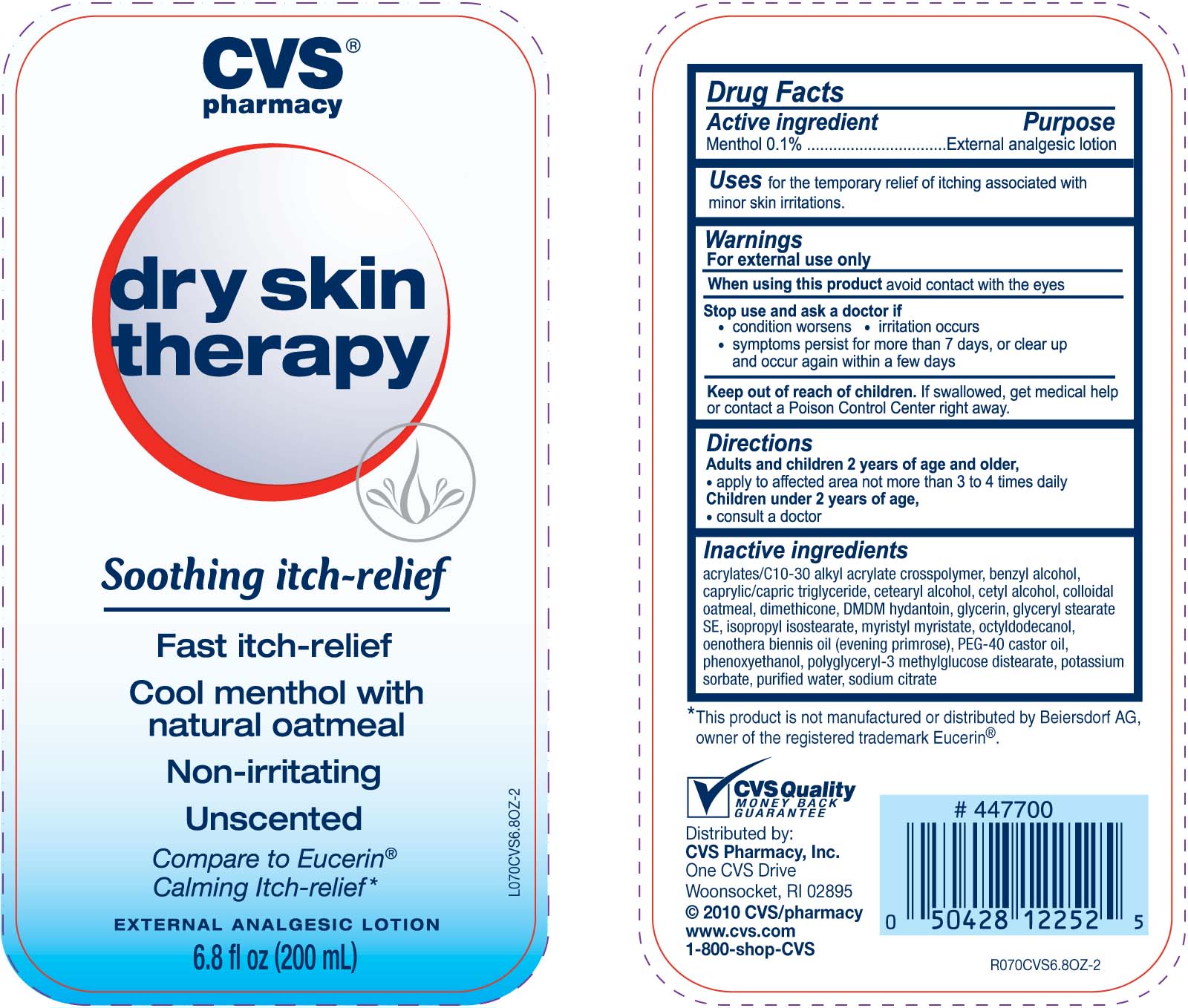 DRUG LABEL: CVS Soothing Itch Relief
NDC: 59779-051 | Form: LOTION
Manufacturer: CVS Pharmacy
Category: otc | Type: HUMAN OTC DRUG LABEL
Date: 20100710

ACTIVE INGREDIENTS: MENTHOL 1 mg/1 mL
INACTIVE INGREDIENTS: WATER; CARBOMER 1342; GLYCERIN; OATMEAL; OCTYLDODECANOL; PROPYLENE GLYCOL DICAPRYLATE/DICAPRATE; ISOPROPYL STEARATE; CETYL ESTERS WAX; CETYL ALCOHOL; STEARYL ALCOHOL; DIMETHICONE 350; GLYCERYL MONOSTEARATE; BENZYL ALCOHOL; PHENOXYETHANOL; DMDM HYDANTOIN; ANHYDROUS TRISODIUM CITRATE; CITRIC ACID MONOHYDRATE; EVENING PRIMROSE OIL; POLYOXYL 40 CASTOR OIL; POTASSIUM SORBATE

DRUG FACTS

Active ingredient Purpose
Menthol 0.1%..................................................External analgesic lotion

PURPOSE

Uses for the treatment of itching associated with minor skin irritations.

Keep out of reach of children. If swallowed, get medical help or contact a
Poison Control Center right away.

INDICATIONS AND USAGE

Uses for the treatment of itching associated with minor skin irritations.

Warnings
For external use only
When using this product avoid contact with the eyes
Stop use and ask a doctor if
- condition worsens - irritation occurs
- symptoms persist for more than 7 days, or clear up and occur again within a few days
Keep out of reach of children. If swallowed, get medical help or contact a Poison
Control Center right away. Avoid contact with eyes. If contact occurs, flush thoroughly with water.

Directions
Adults and children 2 years of age and older,
- apply to afected area not more than 3 to 4 times daily
Children under 2 years of age,
- consult a doctor

Inactive Ingredients
acrylates/C10-30 alkyl acrylate crosspolymer, benzyl alcohol, caprylic/capric triglyceride,
cetearyl alcohol, cetyl alcohol, colloidal oatmeal, dimethicone, DMDM hydrantoin, glycerin,
glyceryl stearate SE, isopropyl isostearate, myristyl, myristate, octyldodecanol,
oenothera biennis oil (evening primrose), PEG-40 castor oil, phenoxyethanol,
polyglyceryl-3 methylglucose distearate, potassium sorbate, purified water, sodium citrate